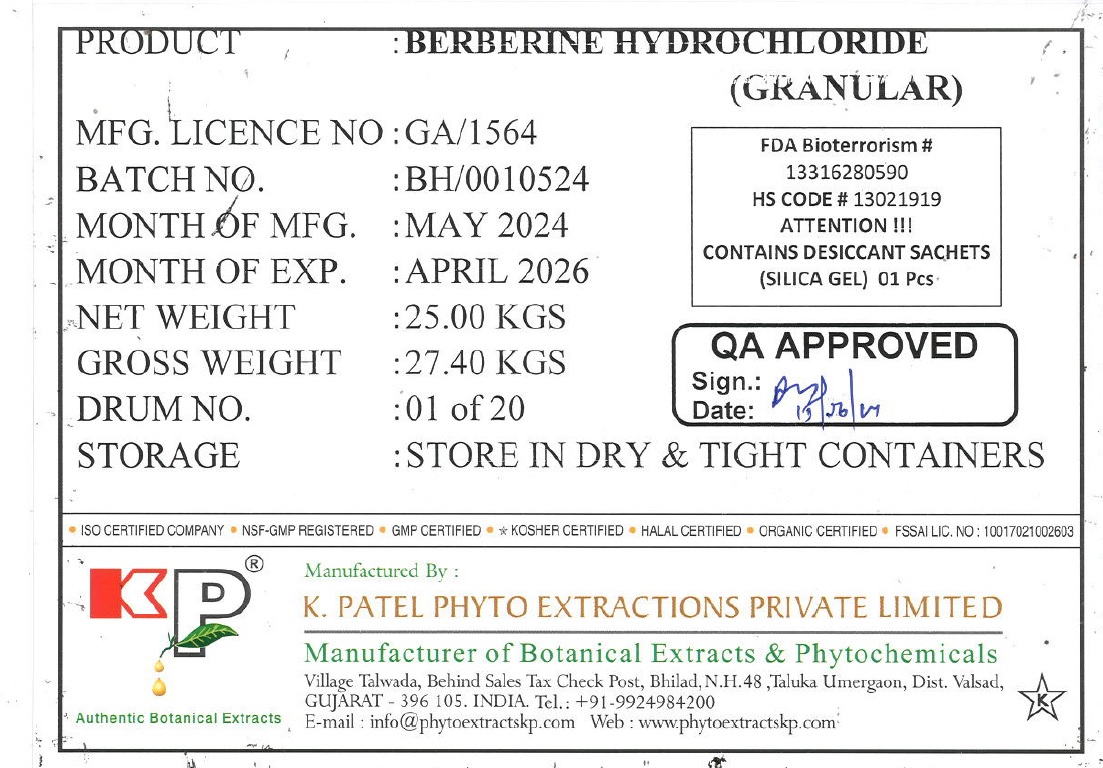 DRUG LABEL: Berberine Hydrochloride
NDC: 73276-003 | Form: GRANULE
Manufacturer: K. Patel Phyto Extractions Private Limited
Category: other | Type: BULK INGREDIENT
Date: 20240617

ACTIVE INGREDIENTS: BERBERINE CHLORIDE 25 kg/25 kg

Berberine Hydrochloride (Granular)